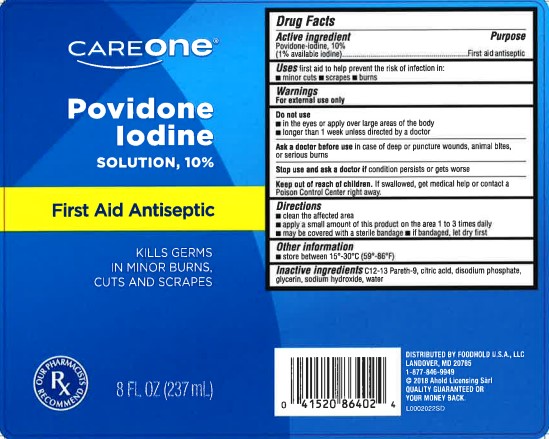 DRUG LABEL: First Aid Antiseptic
NDC: 72476-050 | Form: SOLUTION
Manufacturer: Retail Business Services, LLC
Category: otc | Type: HUMAN OTC DRUG LABEL
Date: 20260206

ACTIVE INGREDIENTS: POVIDONE-IODINE 10 mg/1 mL
INACTIVE INGREDIENTS: C12-13 PARETH-9; CITRIC ACID MONOHYDRATE; SODIUM PHOSPHATE, DIBASIC, ANHYDROUS; GLYCERIN; SODIUM HYDROXIDE; WATER

Care One 050.002/050AE
Povidone-Iodine Solution, 10%

Active ingredient

Povidone-iodine, 10%
(1% available iodine)

Purpose

First aid antiseptic

Uses

first aid to help prevent the risk of infection in: -minor cuts -scrapes -burns

Warnings

For external use only

Do not use

- in the eyes or apply over large areas of the body
- longer than 1 week unless directed by a doctor

Ask a doctor before use

in case of deep or punture wounds, animal bites, or serious burns

Stop use and ask a doctor if

- condition persists or gets worse

Keep out of reach of children.

If swallowed, get medical help or contact a Poison Control Center right away.

Directions

- clean the affected area
- apply a small amount of this product on the area 1 to 3 times daily
- may be covered with a sterile bandage
- If bandaged, let dry first

Other information

- store between 15º-30ºC (59º-86ºF)

Inactive ingredients

C12-13 Pareth-9, citric acid, disodium phosphate, glycerin, sodium hydroxide, water

ADVERSE REACTION

Distributed by Foodhold USA, LLC

Landover, MD 20785

1-877-846-9949

(c) 2018 Ahold Licensing Sarl

Quality guaranteed or your money back

principal display panel

Care One

Povidone Iodine Solution 10%

First Aid Antiseptic

Kills germs in minor burns, cuts and scrapes

Our pharmacists recommend

8 FL OZ (237 mL)